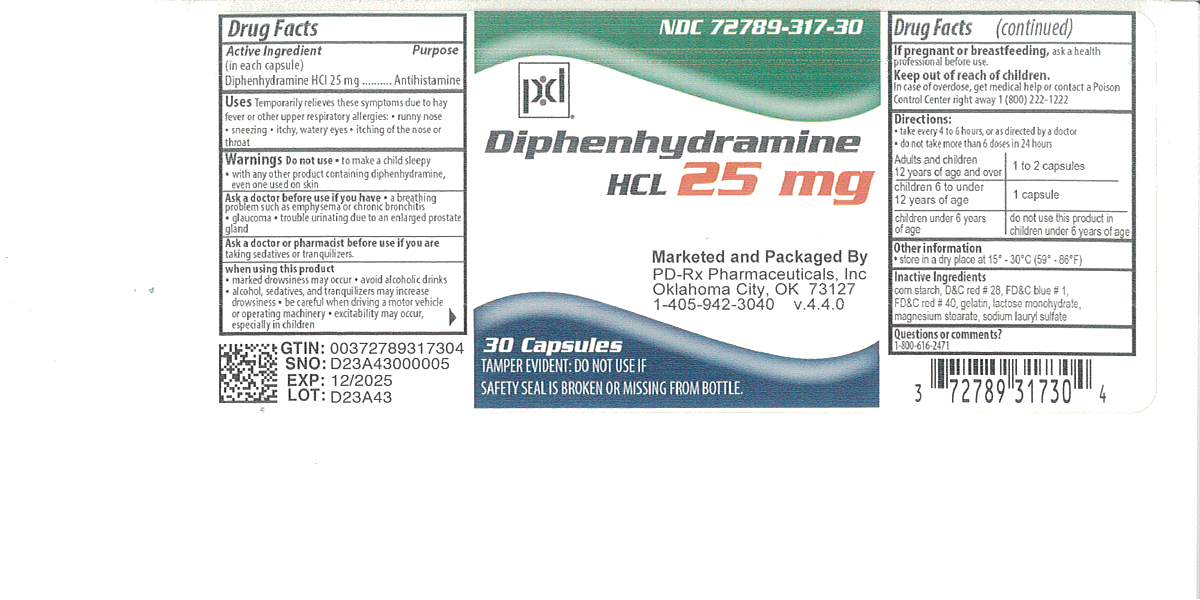 DRUG LABEL: Diphenhydramine Hydrochloride
NDC: 72789-317 | Form: CAPSULE
Manufacturer: PD-Rx Pharmaceuticals, Inc.
Category: otc | Type: HUMAN OTC DRUG LABEL
Date: 20260226

ACTIVE INGREDIENTS: DIPHENHYDRAMINE HYDROCHLORIDE 25 mg/1 1
INACTIVE INGREDIENTS: D&C RED NO. 28; FD&C BLUE NO. 1; FD&C RED NO. 40; MAGNESIUM STEARATE; GELATIN; LACTOSE MONOHYDRATE; SODIUM LAURYL SULFATE; STARCH, CORN

Drug Facts

Active ingredient (in each capsule)
Diphenhydramine HCl 25 mg

Purpose
Antihistamine

Uses

 temporarily relieves these symptoms due to hay fever or other upper respiratory allergies:  runny nose  sneezing  itchy, watery eyes  itching of the nose or throat

 temporarily relieves these symptoms due to the common cold:  runny nose  sneezing

WARNINGS

DO NOT USE

 to make a child sleepy

 with any other product containing diphenhydramine, even one used on skin

Ask a doctor before use if you have
 a breathing problem such as emphysema or chronic bronchitis

 glaucoma
 trouble urinating due to an enlarged prostate gland

Ask a doctor or pharmacist before use if you aretaking sedatives or tranquilizers

When using this product

 marked drowsiness may occur

 avoid alcoholic drinks
 alcohol, sedatives and tranquilizers may increase drowsiness

 be careful when driving a motor vehicle or operating machinery

 excitability may occur, especially in children

PREGNANCY OR BREAST FEEDING

If pregnant or breast-feeding, ask a health professional before use.

Keep out of reach of children.

OVERDOSAGE

In case of overdose, get medical help or contact a Poison Control Center right away (1-800-222-1222).

Directions

 take every 4 to 6 hours, or as directed by a doctor

 do not take more than 6 doses in 24 hours

adults and children 12 years of age and over | 1 to 2 capsules
children 6 to under 12 years of age | 1 capsule
children under 6 years of age | do not use this product in children under 6 years of age

Other information

 store in a dry place at 15° – 30°C (59° – 86°F)

INACTIVE INGREDIENT

corn starch, D&C red #28, FD&C blue #1, FD&C red #40, gelatin, lactose monohydrate, magnesium stearate, sodium lauryl sulfate

Questions or comments?

1-800-616-2471

TAMPER EVIDENT: DO NOT USE IF SAFTY SEAL IS BROKEN OF MISSING FROM BOTTLE
DO NOT USE IF RED CAPSULE BAND IS BROKEN OR MISSING.

PACKAGE LABEL

Diphenhydramin HCl 25 mg

Antihistamine

EACH CAPSULE INDIVIDUALLY
BANDED FOR YOUR PROTECTION